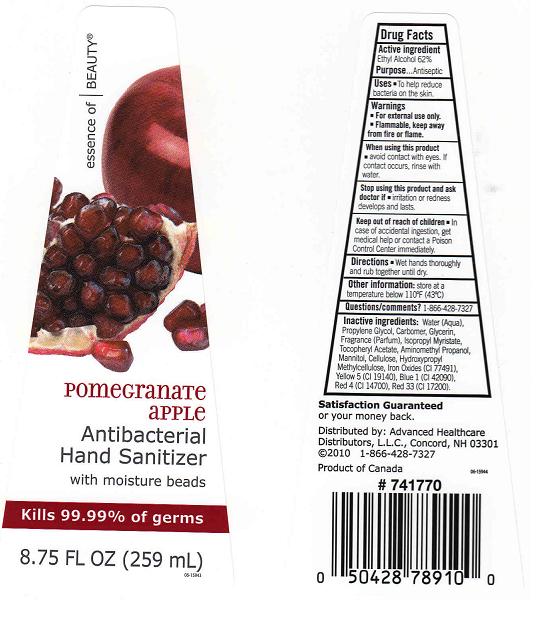 DRUG LABEL: Antibacterial Hand Sanitizer
NDC: 59779-262 | Form: GEL
Manufacturer: CVS Pharmacy Inc
Category: otc | Type: HUMAN OTC DRUG LABEL
Date: 20101008

ACTIVE INGREDIENTS: ALCOHOL 62 mL/100 mL

Drug Facts Box - Back Label

Active Ingredient

Ethyl Alcohol %62

Purpose

Antiseptic

Directions

Wet hands thoroughly and rub together until dry

Warnings

- For external use only.
- Flammable, keep away from fire or flame.

When using this product

Avoid contact with eyes. If contact occurs, rinse with water

Stop using this product and ask doctor if

irritation or redness develops and lasts

Keep out of reach of children

In case of accidental ingestion, get medical help or contact a Poison Control Center immediately

Uses

To help reduce bacteria on the skin

Other information

Store at a temperature below 110oF (43oC)

Inactive Ingredients

Water (Aqua), Propylene Glycol, Carbomer, Glycerin, Fragrance (Parfum), Isopropyl Myristate, Tocopheryl Acetate, Aminomethyl Propanol, Mannitol, Cellulose, Hydroxypropyl Methylcellulose, Iron Oxides (CI 77491), Red 33, Yellow 5 , Blue 1 , Red 4.

Questions/Comments?

1-866-428-7327

Package Front and Back Labels

eb8.jpg